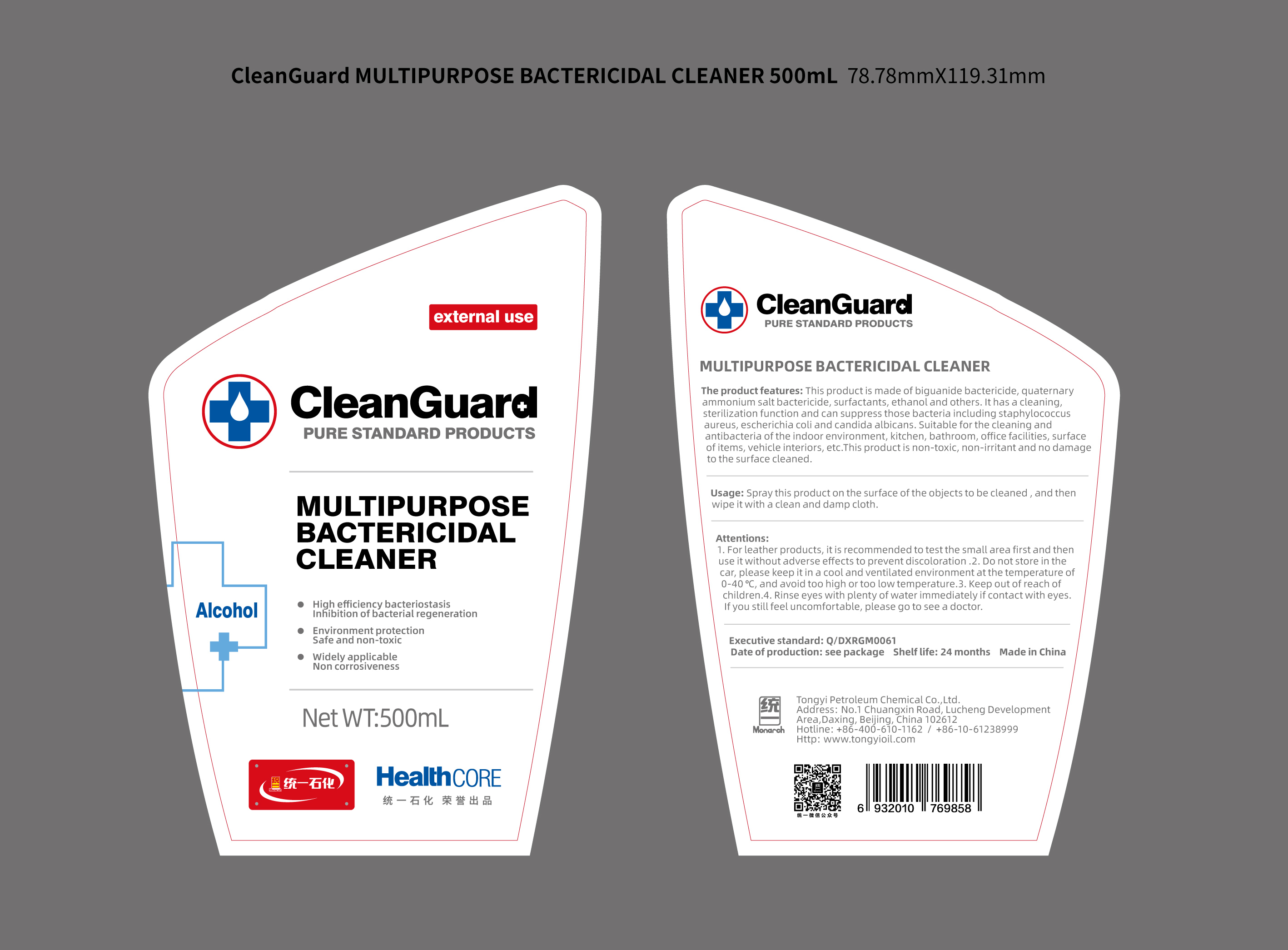 DRUG LABEL: TongYi CleanGuard Multipurpose Bactericidal Cleaner
NDC: 73681-3501 | Form: SPRAY
Manufacturer: Tongyi Petroleum Chemical Co., Ltd.
Category: otc | Type: HUMAN OTC DRUG LABEL
Date: 20200401

ACTIVE INGREDIENTS: ALCOHOL 44.25 mL/150 mL
INACTIVE INGREDIENTS: BENZALKONIUM CHLORIDE 0.75 mL/150 mL; WATER 105 mL/150 mL

TongYi, Multipurpose Bactericidal Cleaner, 500mL *18

Active ingredient

Ethanol

Inactive ingredient

Water

Benzalkonium chloride

Purpose

This product is made of biguanide bactericide, quaternary ammonium salt bactericide, surfactants, ethanol and others. It has a cleaning, sterilization function and can suppress those bacteria including staphylococcus aureus, escherichia coli and candida albicans. Suitable for the cleaning and antibacteria of the indoor environment, kitchen, bathroom, office facilities, surface of items, vehicle interiors, etc. This product is non-toxic, non-irritant and no damage to the surface cleaned.

When using

This product is made of biguanide bactericide, quaternary ammonium salt bactericide, surfactants, ethanol and others. It has a cleaning, sterilization function and can suppress those bacteria including staphylococcus aureus, escherichia coli and candida albicans. Suitable for the cleaning and antibacteria of the indoor environment, kitchen, bathroom, office facilities, surface of items, vehicle interiors, etc. This product is non-toxic, non-irritant and no damage to the surface cleaned.

Do not use

Use only as directed.
Do not use for cases not directed.

Stop use

Stop use if the product's volatile gases cause discomfort, or if you experience respiratory irritation such as cough, asthma, or difficulty breathing.

Ask doctor

If using the product causes serious discomfort, ask or see your doctor.

Ask doctor/pharmacist

If using the product causes serious discomfort, ask or see your doctor/pharmacist.

Keep out of reach of children

Questions

Please contact with us at the phone number +86-10-61238999 when you have any questions.

Pregnancy or breast feeding

Pregnant or breast feeding women shall follow doctor advice.

Indications & usage

Spray this product on the surface of the objects to be cleaned, and then wipe it with a clean and damp cloth.

Dosage & administration

Use it as needed, after following the usage instructions.

For external use only.

Dosage forms & strengths

This product is spray dosage form.
The active ingredient strength is 70%.

Warnings

1. For leather products, it is recommended to test the small area first and then use it without adverse effects to prevent discoloration.

2. Do not store in the car, please keep it in a cool and ventilated environment at the temperature of 0-40 ℃, and avoid too high or too low temperature.

3. Keep out of reach of children.

4. Rinse eyes with plenty of water immediately if contact with eyes. If you still feel uncomfortable, please go to see a doctor.